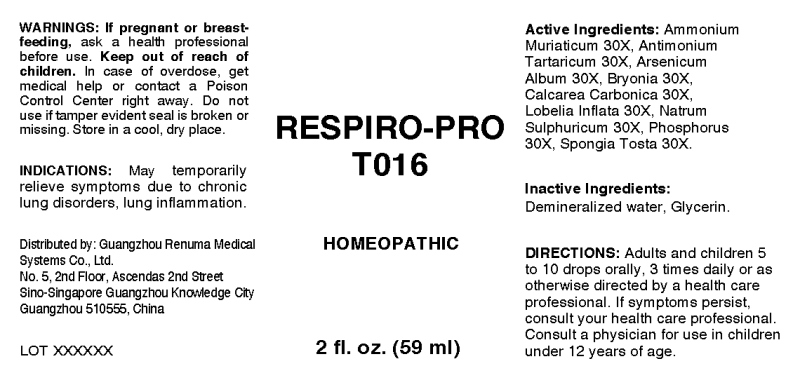 DRUG LABEL: Respiro-Pro
NDC: 71742-0010 | Form: LIQUID
Manufacturer: Guangzhou Renuma Medical Systems Co., Ltd
Category: homeopathic | Type: HUMAN OTC DRUG LABEL
Date: 20171026

ACTIVE INGREDIENTS: AMMONIUM CHLORIDE 30 [hp_X]/1 mL; ANTIMONY POTASSIUM TARTRATE 30 [hp_X]/1 mL; ARSENIC TRIOXIDE 30 [hp_X]/1 mL; BRYONIA ALBA ROOT 30 [hp_X]/1 mL; OYSTER SHELL CALCIUM CARBONATE, CRUDE 30 [hp_X]/1 mL; LOBELIA INFLATA 30 [hp_X]/1 mL; SODIUM SULFATE 30 [hp_X]/1 mL; PHOSPHORUS 30 [hp_X]/1 mL; SPONGIA OFFICINALIS SKELETON, ROASTED 30 [hp_X]/1 mL
INACTIVE INGREDIENTS: WATER; GLYCERIN

Drug Facts:

ACTIVE INGREDIENTS:

Ammonium Muriaticum 30X, Antimonium Tartaricum 30X, Arsenicum Album 30X, Bryonia (Alba) 30X, Calcarea Carbonica 30X, Lobelia Inflata 30X, Natrum Sulphuricum 30X, Phosphorus 30X, Spongia Tosta 30X.

INDICATIONS:

May temporarily relieve symptoms due to chronic lung disorders, lung inflammation.

WARNINGS:

If pregnant or breast-feeding, ask a health professional before use.
Keep out of reach of children. In case of overdose, get medical help or contact a Poison Control Center right away.
Do not use if tamper evident seal is broken or missing.
Store in a cool, dry place.

Keep out of reach of children. In case of overdose, get medical help or contact a Poison Control Center right away.

DIRECTIONS:

Adults and children 5 to 10 drops orally, 3 times daily or as otherwise directed by a health care professional. If symptoms persist, consult your health care professional.
Consult a physician for use in children under 12 years of age.

INDICATIONS:

May temporarily relieve symptoms due to chronic lung disorders, lung inflammation.

INACTIVE INGREDIENTS:

Demineralized water, Glycerin

QUESTIONS:

Distributed by:
Guangzhou Renuma Medical
Systems Co., Ltd.
No. 5, 2nd Floor, Ascendas 2nd Street
Sino-Singapore Guangzhou Knowledge City
Guangzhou 510555, China

PACKAGE LABEL DISPLAY:

RESPIRO-PRO
T016
HOMEOPATHIC
2 fl. oz. (59 ml)